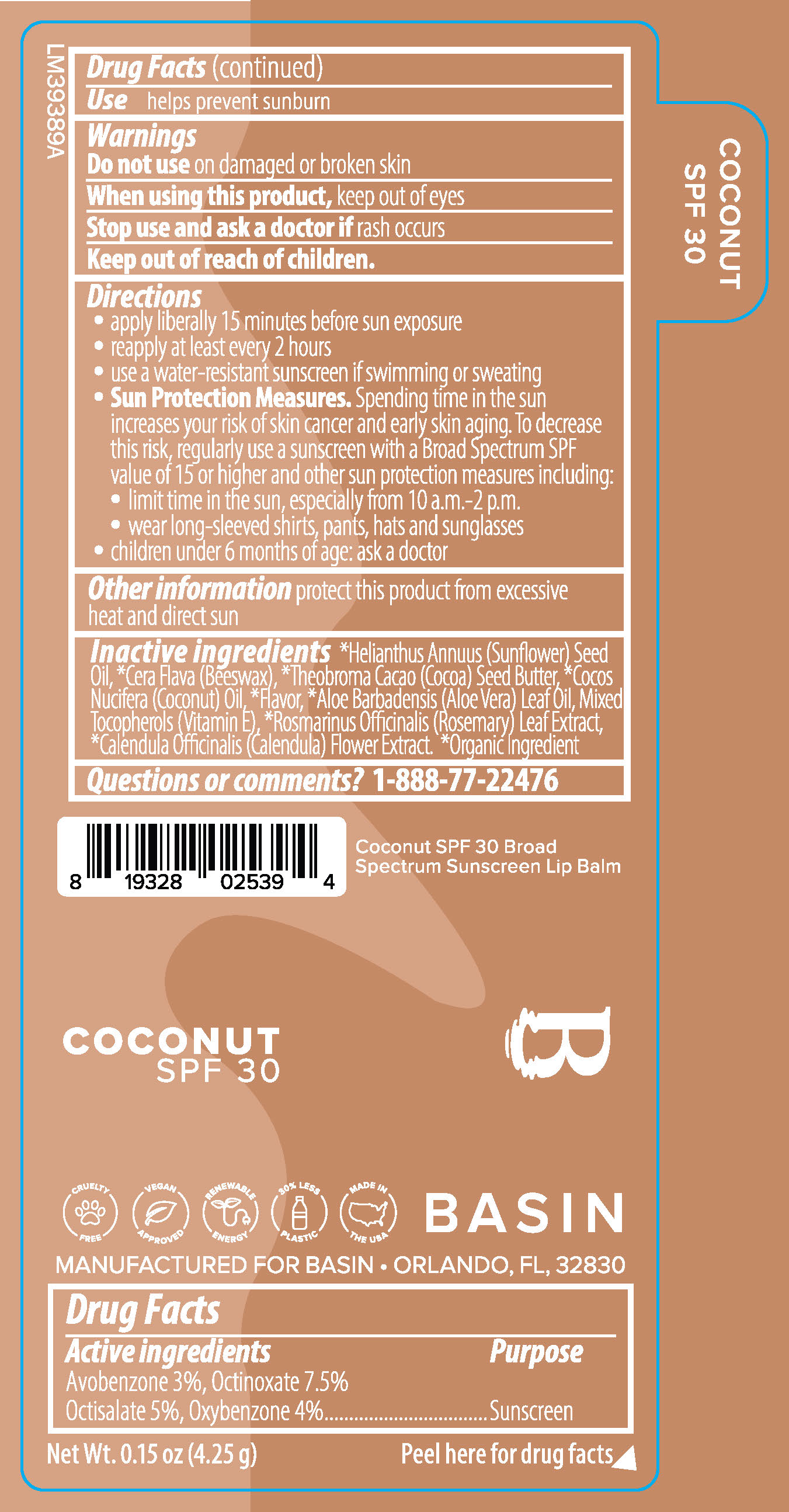 DRUG LABEL: Basin Coconut SPF 30 Lip Balm
NDC: 84603-172 | Form: STICK
Manufacturer: Retail Concepts of Minnesota, Inc.
Category: otc | Type: HUMAN OTC DRUG LABEL
Date: 20260211

ACTIVE INGREDIENTS: OCTINOXATE 7.5 g/100 g; OXYBENZONE 4 g/100 g; AVOBENZONE 3 g/100 g; OCTISALATE 5 g/100 g
INACTIVE INGREDIENTS: ROSEMARY OIL; ALOE VERA LEAF; CALENDULA OFFICINALIS FLOWER; YELLOW WAX; SUNFLOWER OIL; COCOA BUTTER; TOCOPHEROL; COCONUT OIL

172S Basin Coconut SPF 30 Lip Balm

Drug Facts

Active ingredients

Avobenzone 3%, Octinoxate 7.5%

Octisalate 5%, Oxybenzone 4%

Purpose

Sunscreen

INDICATIONS AND USAGE

Usehelps prevent sunburn

Warnings

Do not useon damaged or broken skin

When using this product,keep out of eyes

Stop use and ask a doctor ifrash occurs

Keep out of reach of children.

Directions

- apply liberally 15 minutes before sun exposure
- reapply at least every 2 hours
- use a water-resistant sunscreen if swimming or sweating
- Sun Protection Measures. Spending time in the sun increases your risk of skin cancer and early skin aging. To decrease this risk, regularly use a sunscreen with a Broad Spectrum SPF value of 15 or higher and other sun protection measures including:
- limit time in the sun, especially from 10 a.m. - 2 p.m.
- wear long-sleeved shirts, pants, hats and sunglasses
- children under 6 months of age: ask a doctor

STORAGE AND HANDLING

Other informationprotect this product from excessive heat and direct sun

INACTIVE INGREDIENT

Inactive ingredients*Helianthus Annuus (Sunflower) Seed Oil, *Cera Flava (Beeswax), *Theobroma Cacao (Cocoa) Seed Butter, *Cocos Nucifera (Coconut) Oil, *Flavor, *Aloe Barbadensis (Aloe Vera) Leaf Oil, Mixed Tocopherols (Vitamin E), *Rosmarinus Officinalis (Rosemary) Leaf Extract, *Calendula Officinalis (Calendula) Flower Extract. *Organic Ingredient

Questions or comments?1-888-77-22476

Coconut SPF 30 Broad

Spectrum Sunscreen Lip Balm

Coconut

SPF 30

Cruelty Free Vegan Approved Renewable Energy 30% Less Plastic Made in the USA

Basin

Manufactured for Basin • Orlando, FL, 32830

Net Wt. 0.15 oz (4.25 g) Peel here for drug facts

Coconut

SPF 30

PACKAGE LABEL

Net Wt. .15oz (4.25g)